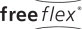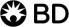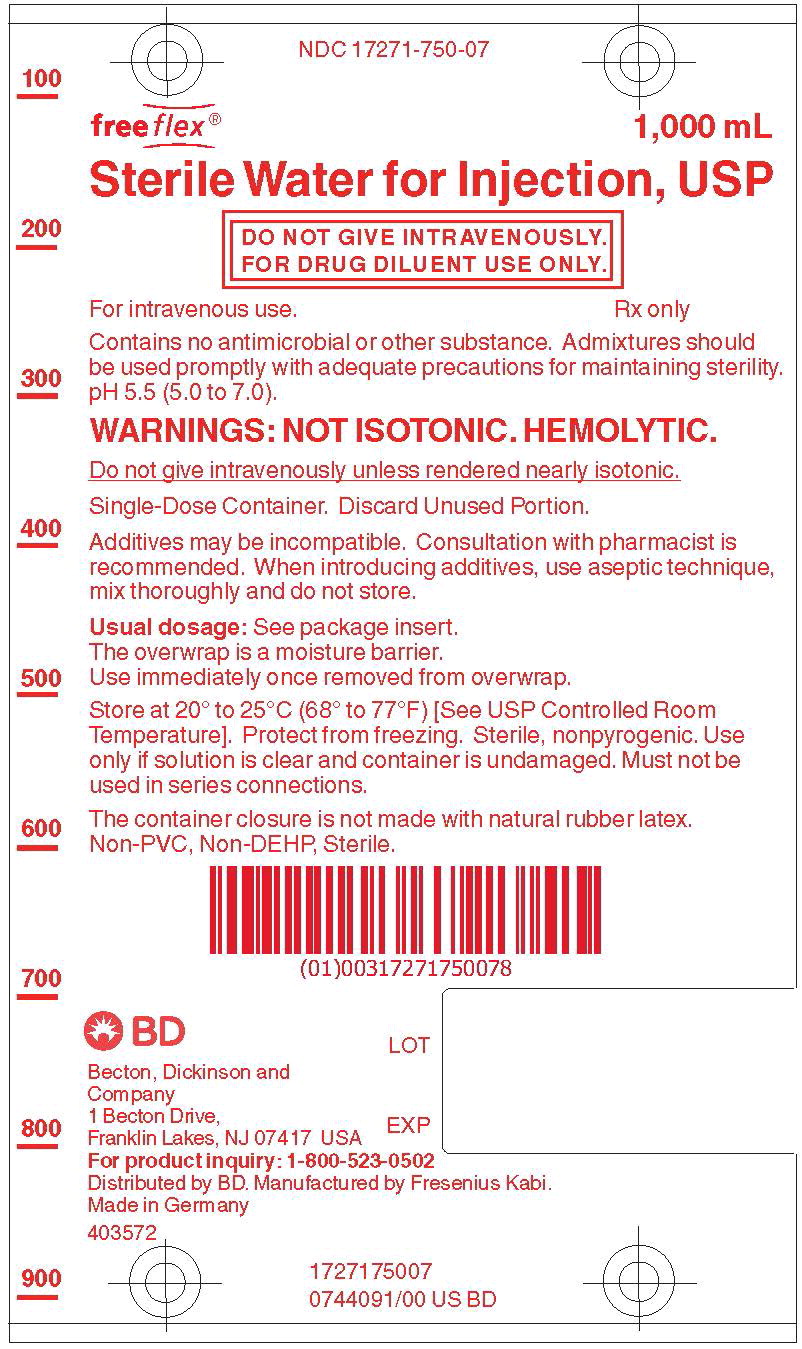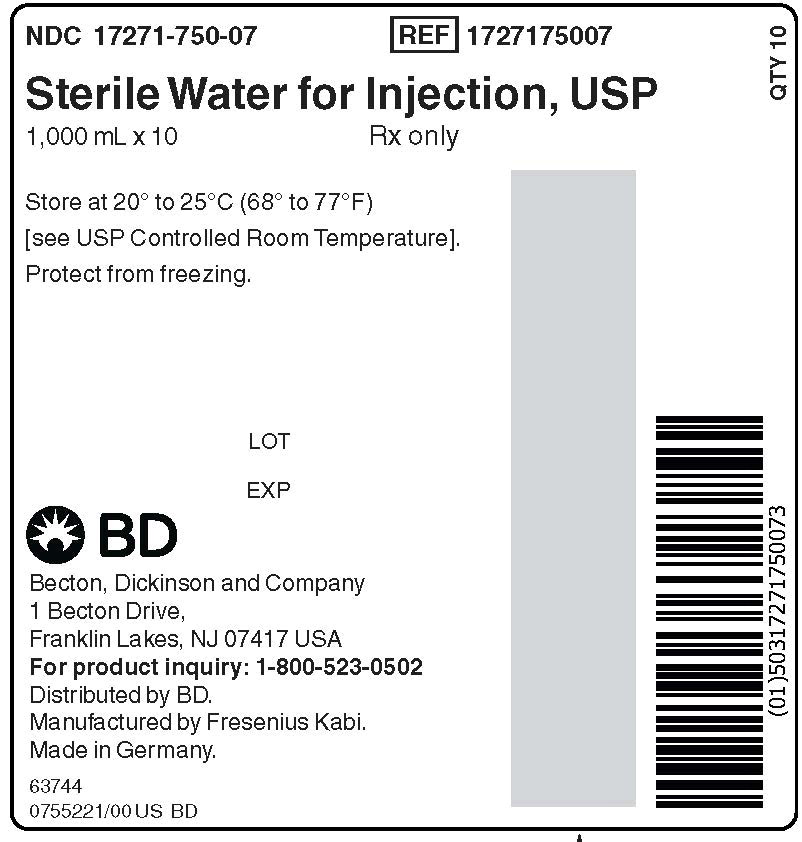 DRUG LABEL: Sterile Water

NDC: 17271-750 | Form: INJECTION, SOLUTION
Manufacturer: Becton Dickinson and Company

Category: prescription | Type: HUMAN PRESCRIPTION DRUG LABEL
Date: 20240531

ACTIVE INGREDIENTS: WATER
 1000 mL/1000 mL

Sterile Water for Injection, USP

FOR DRUG DILUENT USE ONLY

Rx only

DESCRIPTION:

Sterile Water for Injection, USP is a sterile, nonpyrogenic, solute-free preparation of distilled water for injection. It is for use only as a sterile solvent or diluent vehicle for drugs or solutions suitable for parenteral administration. The pH is 5.5 (5.0 to 7.0).

Sterile Water for Injection contains no bacteriostat, antimicrobial agent or added

buffer and is intended only for single dose injection after admixture with an appropriate solute or solution. When smaller amounts are required, the unused portion should be discarded.

Sterile Water for Injection is a pharmaceutic aid (vehicle) and parenteral fluid replenisher after addition of an appropriate solute.

Water for Injection, USP is chemically designated H2O.

The flexible container is fabricated from a specially formulated non-plasticized, film

containing polypropylene and thermoplastic elastomers (freeflex® bag). The amount of water that can permeate from the container into the overwrap is insufficient to affect the solution significantly. Solutions in contact with the flexible container can leach out certain of the container's chemical components in very small amounts within the expiration period. The suitability of the container material has been confirmed by tests in animals according to USP biological tests for plastic containers.

CLINICAL PHARMACOLOGY:

When administered intravenously as a vehicle for drugs, sterile water for injection provides a source of water for parenteral fluid replenishment after sufficient solute is introduced to achieve an osmolarity of 112 mOsmol or more per liter.

Water is an essential constituent of all body tissues and accounts for approximately 70% of total body weight. Average normal adult daily requirement ranges from two to three liters (1.0 to 1.5 liters each for insensible water loss by perspiration and urine production).

Water balance is maintained by various regulatory mechanisms. Water distribution depends primarily on the concentration of electrolytes in the body compartments and sodium (Na^+) plays a major role in maintaining physiologic equilibrium.

INDICATIONS AND USAGE:

Sterile Water for Injection is indicated for use only as a solvent or diluent vehicle for parenterally administered drugs or solutions and as a source of water for parenteral fluid replenishment after suitable additives are introduced.

For intravenous administration, an osmolar concentration not less than two-fifths (0.4) of the normal osmolarity of the extracellular fluid (280 mOsmol/liter) is essential to avoid intravascular hemolysis.

CONTRAINDICATIONS:

Do not administer without the addition of a solute.

WARNINGS:

FOR DRUG DILUENT USE ONLY.

Intravenous administration of Sterile Water for Injection without additives may result in hemolysis.

The intravenous administration of sterile water for injection with additives can cause fluid and/or solute overloading resulting in dilution of serum electrolyte concentrations, overhydration, congested states or pulmonary edema. The risk of dilutional states is inversely proportional to the electrolyte concentrations of administered parenteral solutions. The risk of solute overload causing congested states with peripheral and pulmonary edema is directly proportional to the electrolyte concentrations of such solutions.

WARNING: This product contains aluminum that may be toxic. Aluminum may reach toxic levels with prolonged parenteral administration if kidney function is impaired. Premature neonates are particularly at risk because their kidneys are immature, and they require large amounts of calcium and phosphate solutions, which contain aluminum.

Research indicates that patients with impaired kidney function, including premature neonates, who receive parenteral levels of aluminum at greater than 4 to 5 mcg/kg/day accumulate aluminum at levels associated with central nervous system and bone toxicity.

Tissue loading may occur at even lower rates of administration.

PRECAUTIONS:

Do not use for intravenous injection unless the osmolar concentration of additives totals at least 112 mOsmol/liter (two-fifths of the normal osmolarity of the extracellular fluid - 280 mOsmol/liter).

Do not administer unless solution is clear and container is undamaged. Discard unused portion.

Pregnancy Category C

Animal reproduction studies have not been conducted with sterile water for injection. It is also not known whether sterile water containing additives can cause fetal harm when administered to a pregnant woman or can affect reproduction capacity. Sterile water for injection with additives should be given to a pregnant woman only if clearly needed.

Pediatric Use

The safety and effectiveness in the pediatric population are based on the similarity of the clinical conditions of the pediatric and adult populations. In neonates or very small infants the volume of fluid may affect fluid and electrolyte balance.

This product contains no more than 25 mcg/L of aluminum.

ADVERSE REACTIONS:

Reactions which may occur because of the technique of administration include febrile response, infection at the site of injection, venous thrombosis or phlebitis extending from the site of injection, extravasation and hypervolemia.

If an adverse reaction does occur, discontinue the infusion, evaluate the patient, institute appropriate therapeutic countermeasures and save the remainder of the fluid for examination if deemed necessary.

OVERDOSAGE:

In the event of overhydration or solute overload, re-evaluate the patient and institute appropriate corrective measures (See WARNINGS).

DOSAGE AND ADMINISTRATION:

Following suitable admixture of prescribed additive, the dose is usually dependent upon the age, weight and clinical condition of the patient.

Drug Interactions

Additives may be incompatible. Consult with pharmacist, if available. When introducing additives, use aseptic technique, mix thoroughly and do not store.

Parenteral drug products should be inspected visually for particulate matter and discoloration prior to administration, whenever solution and container permit (See PRECAUTIONS).

HOW SUPPLIED:

Sterile Water for Injection, USP is supplied in a single dose flexible plastic container as follows:

Product No. | NDC No. | Bag Size | Bags Per Carton
1727175007 | 17271-750-07 | 1,000 mL Bag | 10 Bags

The container closure is not made with natural rubber latex. Non-PVC, Non-DEHP, Sterile.

INSTRUCTIONS FOR USE:

Check flexible container solution composition, lot number, and expiry date.

Do not remove solution container from its overwrap until immediately before use. Use sterile equipment and aseptic technique.

To Open

1. Turn solution container over so that the text is face down. Using the pre-cut corner tabs, peel open the overwrap and remove solution container.
2. Check the solution container for leaks by squeezing firmly. If leaks are found, or if the seal is not intact, discard the solution.
3. Do not use if the solution is cloudy or a precipitate is present.

To Add Medication

1. Identify WHITE Additive Port with arrow pointing toward container.
2. Immediately before injecting additives, break off WHITE Additive Port Cap with the arrow pointing toward container.
3. Hold base of WHITE Additive Port horizontally.
4. Insert needle horizontally through the center of WHITE Additive Port's septum and inject additives.
5. Mix container contents thoroughly.

Preparation for Administration

1. Immediately before inserting the infusion set, break off BLUE Infusion Port Cap with the arrow pointing away from container.
2. Use a non-vented infusion set or close the air-inlet on a vented set.
3. Close the roller clamp of the infusion set.
4. Hold the base of BLUE Infusion Port.
5. Insert spike through BLUE Infusion Port by rotating wrist slightly until the spike is inserted.

NOTE: See full directions accompanying administration set.

WARNING: DO NOT USE FLEXIBLE CONTAINER IN SERIES CONNECTIONS.

Store at 20° to 25°C (68° to 77°F) [See USP Controlled Room Temperature].

Protect from freezing.

Manufactured for:

Becton, Dickinson and Company
1 Becton Drive,
Franklin Lakes, NJ 07417 USA
For product inquiry: 1-800-523-0502
Distributed by BD. Manufactured by Fresenius Kabi.

Made in Germany.

451640

Issued: June 2019

PACKAGE LABEL

PACKAGE LABEL - PRINCIPAL DISPLAY – Sterile Water for Injection Bag Label
NDC 17271-750-07
freeflex® 1,000 mL

Sterile Water for Injection, USP

DO NOT GIVE INTRAVENOUSLY.

FOR DRUG DILUENT USE ONLY.

For intravenous use.

Rx only

PACKAGE LABEL

PACKAGE LABEL - PRINCIPAL DISPLAY – Sterile Water for Injection Case Label
NDC 17271-750-07 REF 1727175007
Sterile Water for Injection, USP

1,000 mL x 10 Rx only